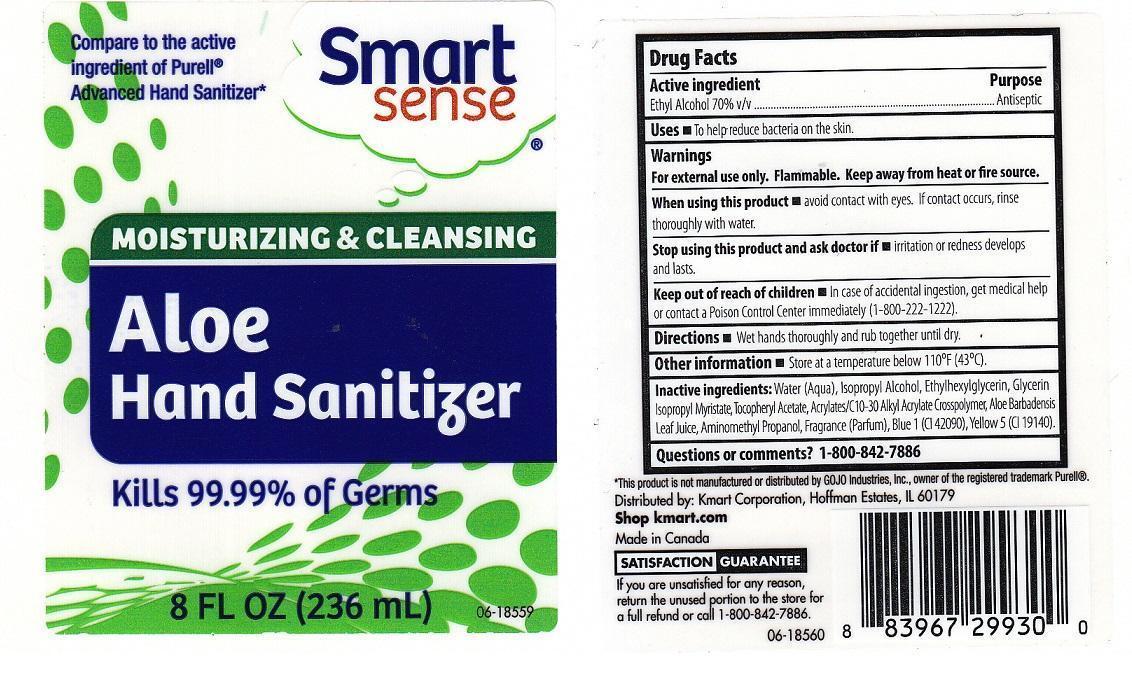 DRUG LABEL: SMART SENSE
NDC: 49738-079 | Form: LIQUID
Manufacturer: KMARTK CORPORATION
Category: otc | Type: HUMAN OTC DRUG LABEL
Date: 20131107

ACTIVE INGREDIENTS: ALCOHOL 700 mg/1 mL
INACTIVE INGREDIENTS: WATER; ISOPROPYL ALCOHOL; ETHYLHEXYLGLYCERIN; GLYCERIN; ISOPROPYL MYRISTATE; .ALPHA.-TOCOPHEROL ACETATE; CARBOMER COPOLYMER TYPE A (ALLYL PENTAERYTHRITOL CROSSLINKED); ALOE VERA LEAF; AMINOMETHYLPROPANOL; FD&C BLUE NO. 1; FD&C YELLOW NO. 5

DRUG FACTS

ACTIVE INGREDIENT

ETHYL ALCOHOL 70% V/V

PURPOSE

ANTISEPTIC

USES

TO HELP REDUCE BACTERIA ON THE SKIN

WARNINGS

FOR EXTERNAL USE ONLY. FLAMMABLE. KEEP AWAY FROM HEAT OR FIRE SOURCE

WHEN USING THIS PRODUCT

AVOID CONTACT WITH EYES. IF CONTACT OCCURS, RINSE THOROUGHLY WITH WATER

STOP USING THIS PRODUCT AND ASK DOCTOR IF

IRRITATION OR REDNESS DEVELOPS AND LASTS

KEEP OUT OF REACH OF CHILDREN

IN CASE OF ACCIDENTAL INGESTION, GET MEDICAL HELP OR CONTACT A POISON CONTROL CENTER IMMEDIATELY (1-800-222-1222)

DIRECTIONS

WET HANDS THOROUGHLY AND RUB TOGETHER UNTIL DRY

OTHER INFORMATION

STORE AT A TEMPERATURE BELOW 110°F (43°C)

INACTIVE INGREDIENTS

WATER (AQUA), ISOPROPYL ALCOHOL, ETHYLHEXYLGLYCERIN, GLYCERIN, ISOPROPYL MYRISTATE, TOCOPHERYL ACETATE, ACRYLATES/C10-30 ALKYL ACRYLATE CROSSPOLYMER, ALOE BARBADENSIS LEAF JUICE, AMINOMETHYL PROPANOL, FRAGRANCE (PARFUM), BLUE 1 (CI 42090), YELLOW 5 (CI 19140)

QUESTIONS OR COMMENTS?

1-800-842-7886